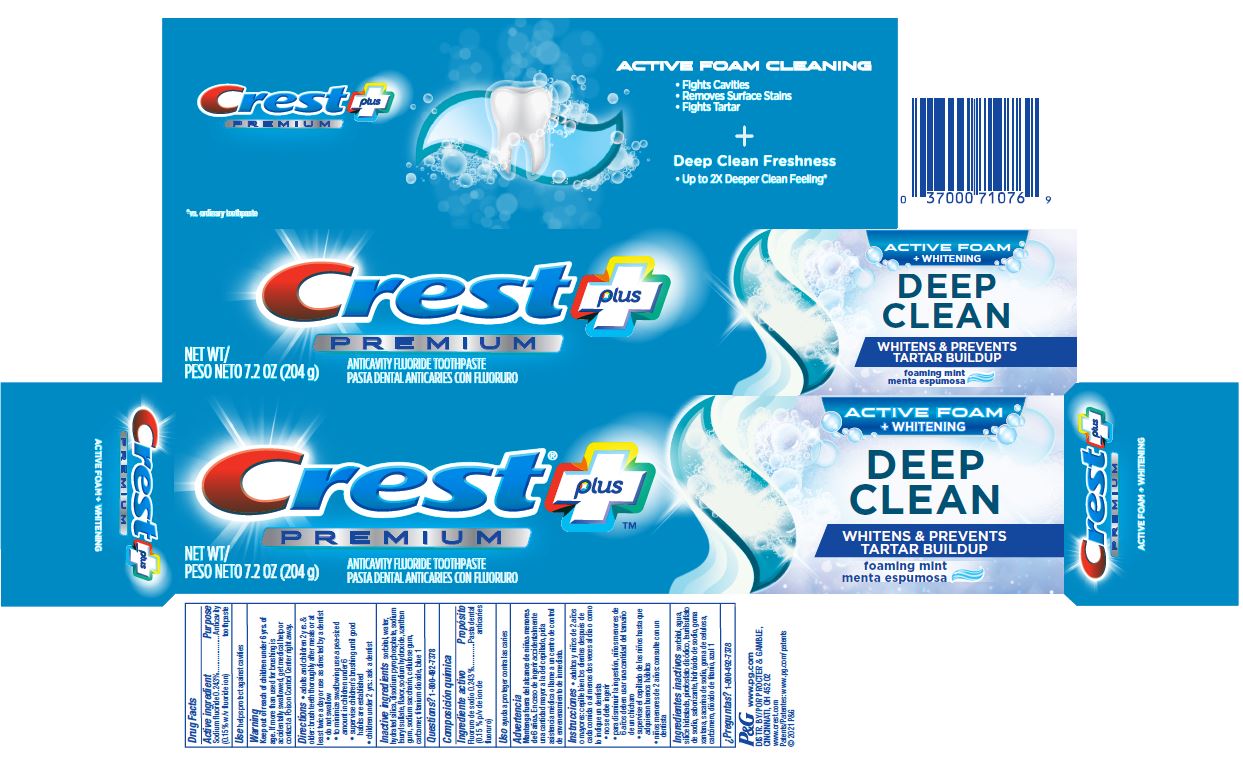 DRUG LABEL: Crest Premium Plus
NDC: 37000-994 | Form: PASTE, DENTIFRICE
Manufacturer: The Procter & Gamble Manufacturing Company
Category: otc | Type: HUMAN OTC DRUG LABEL
Date: 20250701

ACTIVE INGREDIENTS: SODIUM FLUORIDE 1.5 mg/1 g
INACTIVE INGREDIENTS: XANTHAN GUM; TITANIUM DIOXIDE; FD&C BLUE NO. 1; WATER; SORBITOL; HYDRATED SILICA; SODIUM ACID PYROPHOSPHATE; SODIUM LAURYL SULFATE; CARBOXYMETHYLCELLULOSE SODIUM, UNSPECIFIED FORM; SODIUM HYDROXIDE; SACCHARIN SODIUM; CARBOXYPOLYMETHYLENE

Crest Premium Plus Deep Clean Active Foam

Drug Facts

Active ingredient

Sodium fluoride 0.243% (0.15% w/v fluoride ion)

Purpose

Anticavity toothpaste

Use

helps protect against cavities

Warning

Keep out of reach of children under 6 yrs. of age. If more than used for brushing is accidentally swallowed, get medical help or contact a Poison Control Center right away.

Directions

- adults and children 2 yrs. & older: brush teeth thoroughly after meals or at least twice a day or use as directed by a dentist
- do not swallow
- to minimize swallowing use a pea-sized amount in children under 6
  - supervise children's brushing until good habits are established
- children under 2 yrs.: ask a dentist

Inactive ingredients

sorbitol, water, hydrated silica, disodium pyrophosphate, sodium lauryl sulfate, flavor, sodium hydroxide, xanthan gum. sodium saccharin, cellulose gum, carbomer, titanium dioxide, blue 1

Questions?

1-800-492-7378

DISTR. BY PROCTER & GAMBLE, CINCINNATI, OH 45202

PRINCIPAL DISPLAY PANEL - 204 g Tube Carton

Crest ® plus

PREMIUM
ANTICAVITY FLUORIDE TOOTHPASTE

NET WT 7.2 OZ (204 g)
ACTIVE FOAM

+ WHITENING

DEEP CLEAN

WHITENS & PREVENTS TARTAR BUILDUP

foaming mint